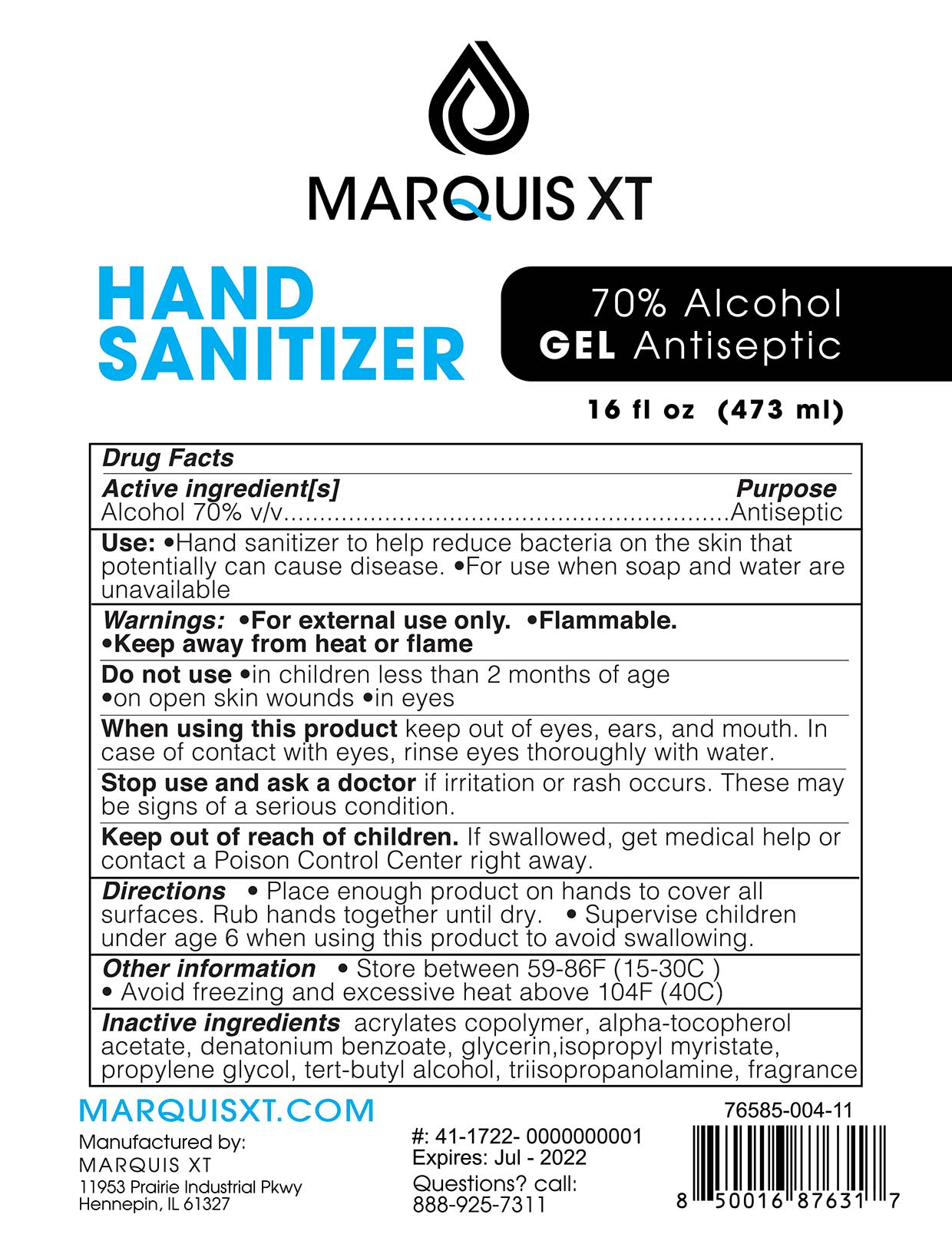 DRUG LABEL: Hand Sanitizer
NDC: 76585-004 | Form: GEL
Manufacturer: Marquis Extraction Technology LLC
Category: otc | Type: HUMAN OTC DRUG LABEL
Date: 20200630

ACTIVE INGREDIENTS: ALCOHOL 80 mL/100 mL
INACTIVE INGREDIENTS: METHACRYLIC ACID - ETHYL ACRYLATE COPOLYMER (4500 MPA.S) 5 mL/100 mL; ALPHA-TOCOPHEROL 0.005 mL/100 mL; FRAGRANCE LAVENDER & CHIA F-153480 0.6 mL/100 mL; GLYCERIN 1.25 mL/100 mL; ISOPROPYL MYRISTATE 0.2 mL/100 mL; WATER; PROPYLENE GLYCOL 0.75 mL/100 mL; TRIISOPROPYLAMINE 0.875 mL/100 mL; CUMINYL ACETALDEHYDE 0.6 mL/100 mL; LINALOOL, (+)- 0.6 mL/100 mL

Active Ingredient(s)

Alcohol 70% v/v. Purpose: Antiseptic

Purpose

Antiseptic, Hand Sanitizer

Use

Hand Sanitizer to help reduce bacteriaon the skin that potentially can cause disease. For use when soap and water are unavailable

Warnings

For external use only. Flammable. Keep away from heat or flame

Do not use

- in children less than 2 months of age
- on open skin wounds
- in eyes

When using this product keep out of eyes, ears, and mouth. In case of contact with eyes, rinse eyes thoroughly with water.
Stop use and ask a doctor if irritation or rash occurs. These may be signs of a serious condition.
Keep out of reach of children. If swallowed, get medical help or contact a Poison Control Center right away.

Stop use and ask a doctor if irritation or rash occurs. These may be signs of a serious condition.

Keep out of reach of children. If swallowed, get medical help or contact a Poison Control Center right away.

Directions

- Place enough product on hands to cover all surfaces. Rub hands together until dry.
- Supervise children under 6 years of age when using this product to avoid swallowing.

Other information

- Store between 15-30C (59-86F)
- Avoid freezing and excessive heat above 40C (104F)

Inactive ingredients

acrylates copolymer, alpha tocopherol acetate, Denatonium benzoate, glycerin, isopropyl myristate propylene glycol, triisopropyl amine, fragrance

Package Label - Principal Display Panel

NDC: 76585-004